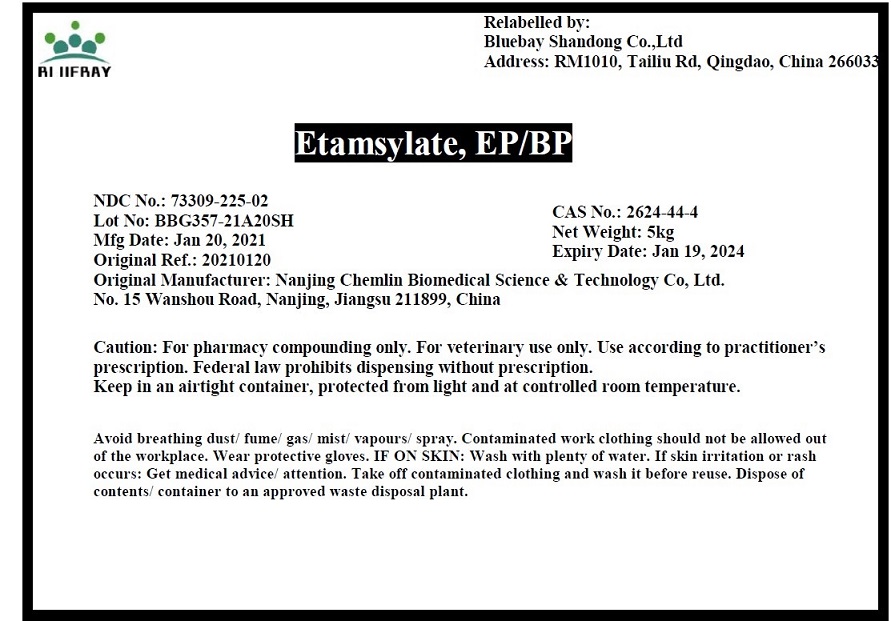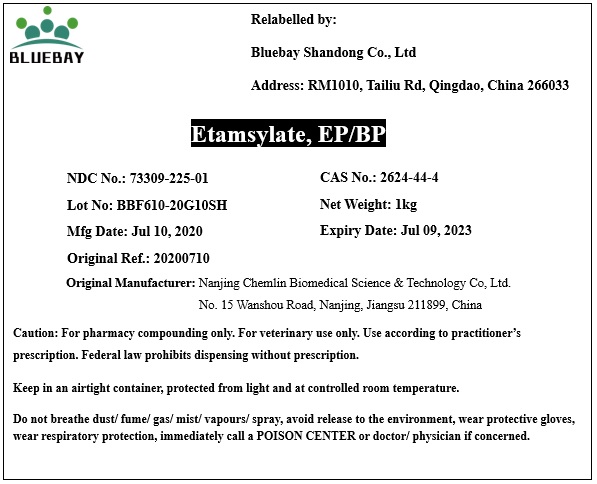 DRUG LABEL: Etamsylate
NDC: 73309-225 | Form: POWDER
Manufacturer: BLUEBAY SHANDONG CO.,LTD
Category: other | Type: BULK INGREDIENT
Date: 20210702

ACTIVE INGREDIENTS: ETHAMSYLATE 1 kg/1 kg

Etamsylate